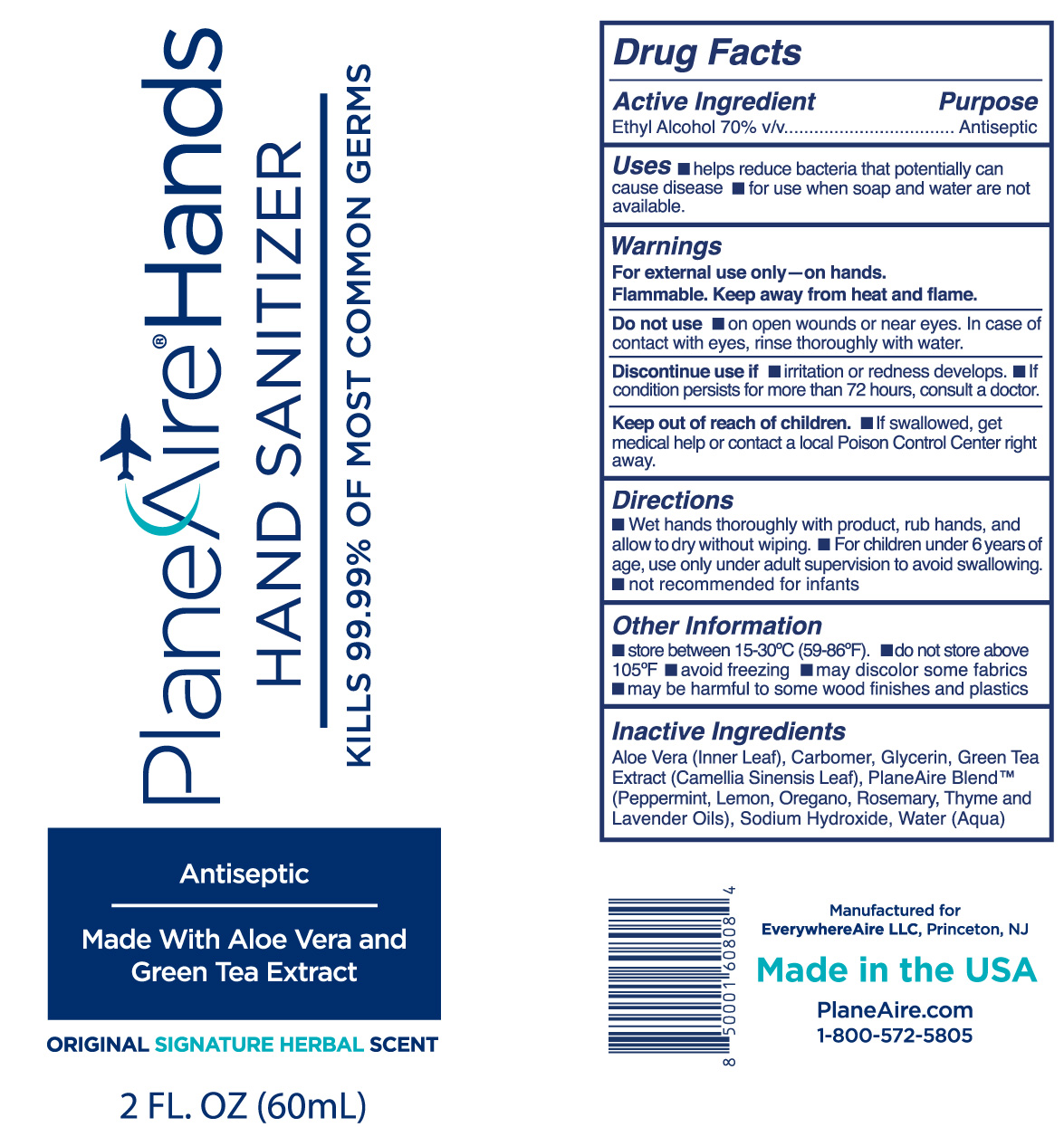 DRUG LABEL: PlaneAireHands hand sanitizer
NDC: 80335-104 | Form: GEL
Manufacturer: EverywhereAire LLC
Category: otc | Type: HUMAN OTC DRUG LABEL
Date: 20211008

ACTIVE INGREDIENTS: ALCOHOL 70 mL/100 mL
INACTIVE INGREDIENTS: GREEN TEA LEAF; THYMUS VULGARIS LEAF; OREGANO LEAF OIL; LAVENDER OIL; PEPPERMINT OIL; SODIUM HYDROXIDE; GLYCERIN; WATER; ROSEMARY OIL; CARBOMER 980; ALOE VERA LEAF POLYSACCHARIDES; LEMON OIL

PlaneAireHands Hand Sanitizer gel Signature herbal with aloe and green tea

This is a hand sanitizer

Active Ingredient(s)

Ethyl Alcohol 70% v/v.

Purpose

Antiseptic

Use

Helps reduce bacteria that potentially may cause disease. For use when soap and water are not avaiable.

Warnings

For external use only.- hands. Flammable. Keep away from heat or flame

- do not use on open skin wounds or near eyes. In case of contact with eyes, rinse thoroughly with water

When using this product keep out of eyes. In case of contact with eyes, fllush eyes thoroughly with water.
(See Stop use section: Stop use and ask a doctor if irritation or rash lasts for longer than 72 hours)

.
Keep out of reach of children. If swallowed, get medical help or contact a local Poison Control Center right away.

STOP USE

Discontinue use if irritation or rash occurs. If condition persists for more than 72 hours, consult a doctor.

Keep out of reach of children. If swallowed, get medical help or contact Poison Control Center right away.

Directions

- Wet hands thoroughly with product , rub hands, and allow to dry without wiping
- For children under 6 years of age, use only under adult supervision to avoid swallowing
- Not recommended for infants

Other information

- Do not store above 105F
- May discolor some fabrics
- Harmful to wood finishes and plastics

Inactive ingredients

aloe vera inner leaf, green tea extract, carbomer 980, lemon oil, lavender oil, peppermint oil, oregano oil, rosemary oil, thyme oil, sodium hydroxide, water

Indications and Usage helps reduce bacteria that potentially cause disease. For use when soap and water are not available Directions Wet hands thoroughly with product , rub hands, and allow to dry without wiping For children under 6 years of age, use only under adult supervision to avoid swallowing Not recommended for infants

Indications and Usage

To decrease bacteria on skin that could cause diease. Recommended for repeated use.

Dosage and Administration

Wet hands thoroughly with product and allow to dry without wiping
For children under 6, use only under adult supervision
Not recommended for infants

Package Label - Principal Display Panel

2